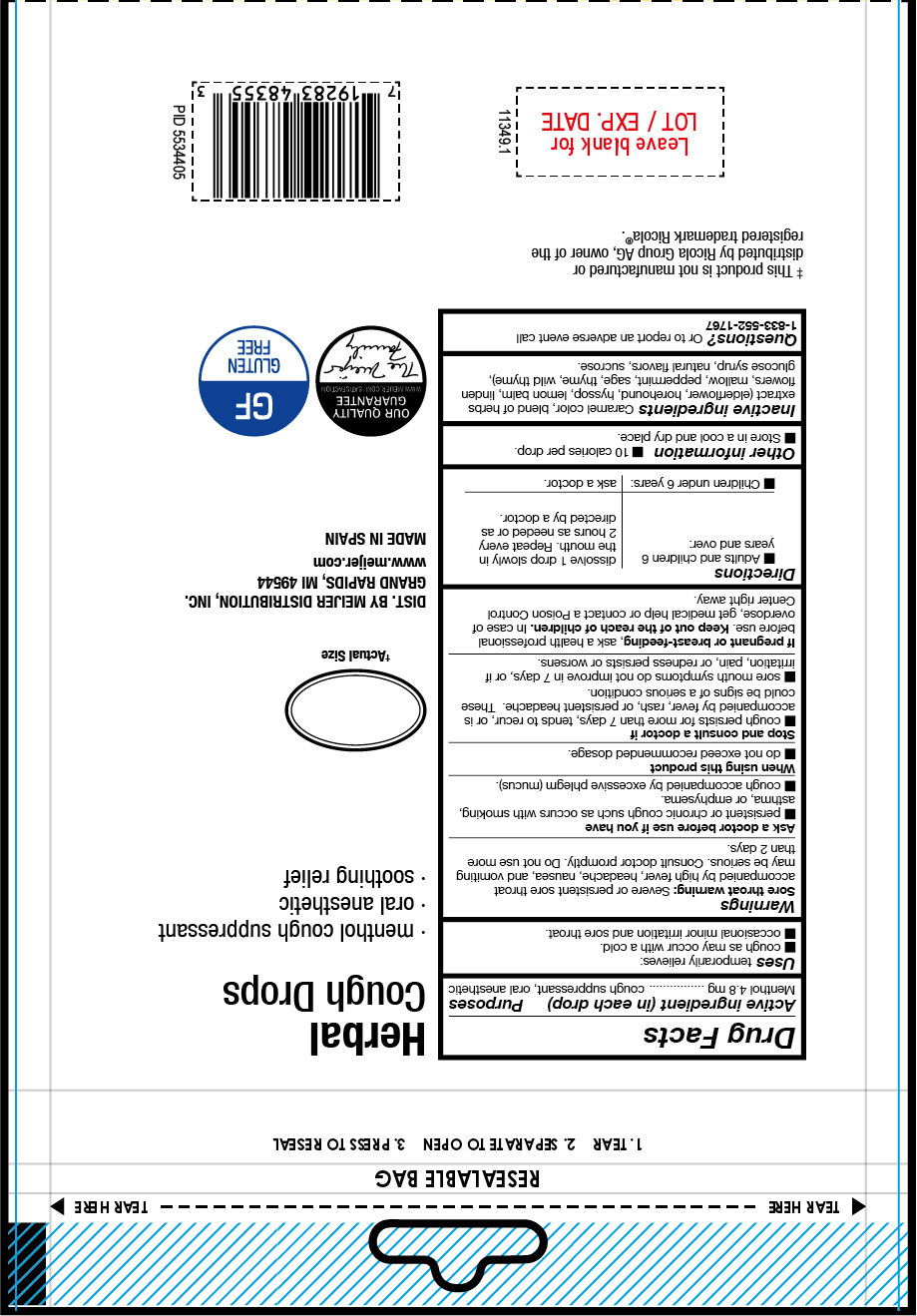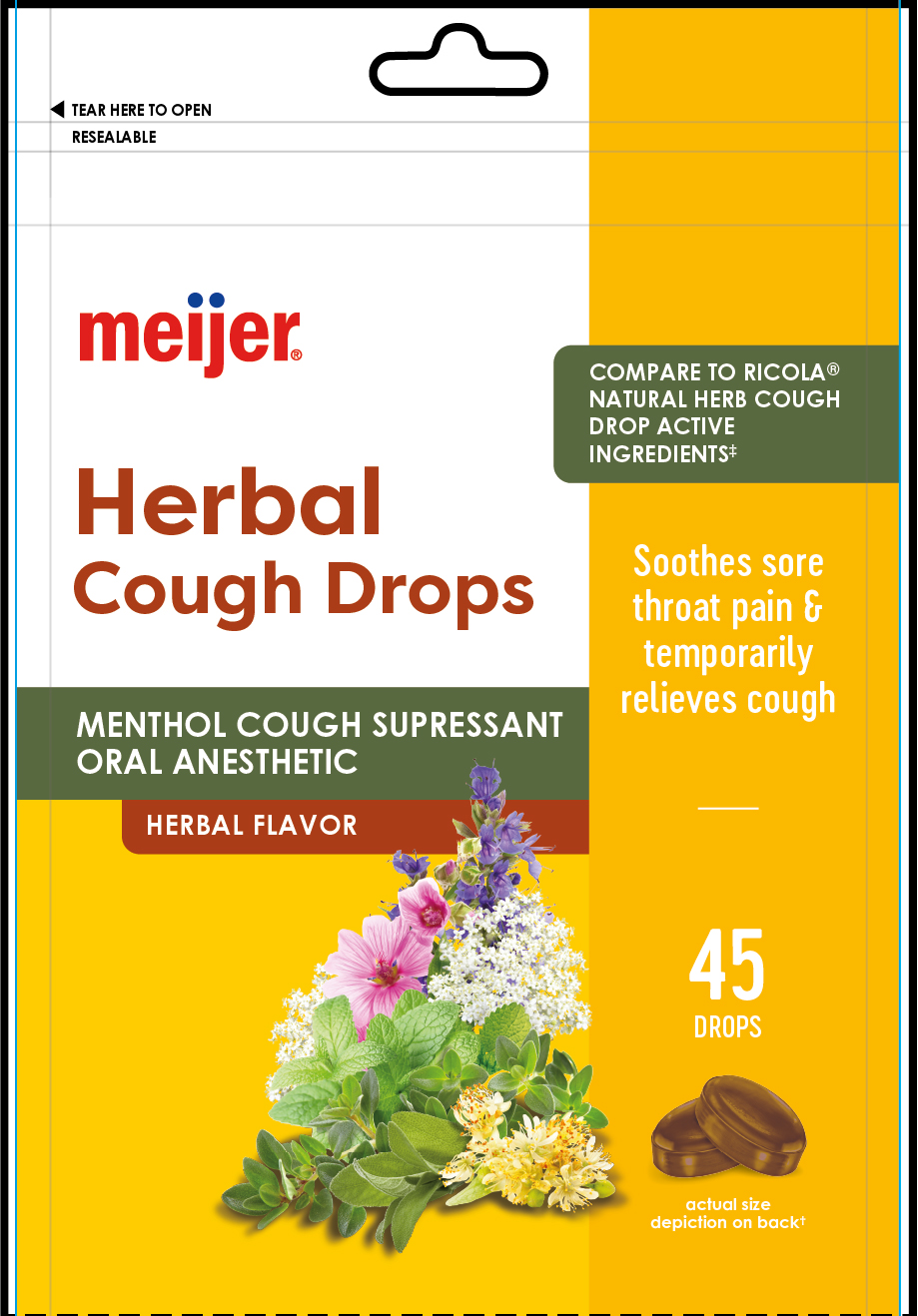 DRUG LABEL: Herbal Cough Drops
NDC: 79481-9968 | Form: PASTILLE
Manufacturer: Meijer, Inc.
Category: otc | Type: HUMAN OTC DRUG LABEL
Date: 20250620

ACTIVE INGREDIENTS: MENTHOL 4.8 mg/1 1
INACTIVE INGREDIENTS: CORN SYRUP; FLAVONE; SAGE; WILD THYME; MALVA SYLVESTRIS (MALLOW) LEAF POWDER; LEMON BALM OIL; HOREHOUND; HYSSOP OIL; LINDEN LEAF; PEPPERMINT; CARAMEL; SUCROSE; THYME

Herbal Throat Drops
Lemon Mint

Active ingredient

- Menthol 1.1 mg

PURPOSE

Uses temporarily relieves:

- coug as may occur with a cold
- occasional minor irritation and sore throat

INDICATIONS AND USAGE

Uses temporarily relieves:

- coug as may occur with a cold
- occasional minor irritation and sore throat

Warnings

Sore throat warning: Severe, persistent sore throat accompanied by fever, headache, nausea, and vomiting may be serious. Consult a doctor promptly. Do not use more than 2 days.

Stop and consult a doctor if

- Cough persists for more than 7 days, tends to recur, or is accompanid by fever, rash or persistent headache. These could be signs of a serious condition.
- Sore mouth symptons do not improve in 7 days, or if irritation, pain or redness persists or worsens.

Stop and consult a doctor if

- Cough persists for more than 7 days, tends to recur, or is accompanid by fever, rash or persistent headache. These could be signs of a serious condition.
- Sore mouth symptons do not improve in 7 days, or if irritation, pain or redness persists or worsens.

PREGNANCY OR BREAST FEEDING

If pregnant or breast-feeding, ask a health professional before use.

Keep out of the reach of children.

OVERDOSAGE

In case of overdose, get medical help or contact a Poison Control Center right away.

Directions

- Adults and children 6 years and over: dissolve 1 drop slowly in mouth. Repeated every 2 hours as needed or as directed by a doctor.
- Children under 6 years: as a doctor

OTHER SAFETY INFORMATION

- Store in a cool and dry place
- 10 calories per drop

INACTIVE INGREDIENT

caramel color, blend of herbs extract (elderflower, horehound, hyssop, lemon balm, liden flowers, mallow, peppermint, sage, thyme, wild thyme), glucose syrup, natural flavors, sucrose.

QUESTIONS

Questions? or to report and adverse event call: 1-833-552-1767

RECENT MAJOR CHANGES

- Indications and Usage
- Dosage and Administration
- Contraindications
- Warnings and Precautions
- Inactive ingredients

Front Package

Front Panel